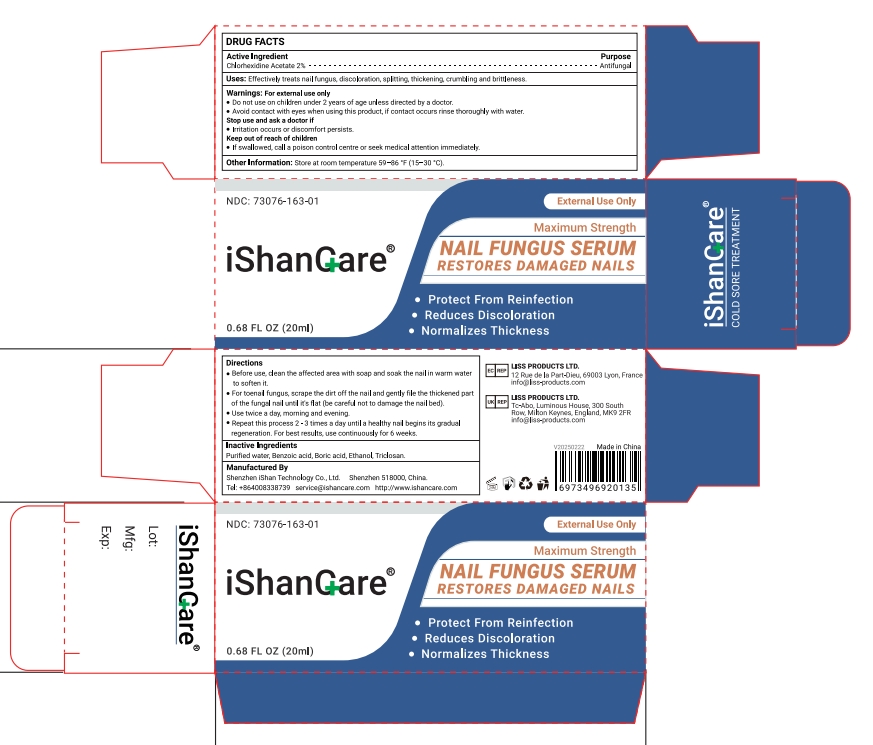 DRUG LABEL: iShancare NAIL FUNGUS SERUM
NDC: 73076-163 | Form: GEL
Manufacturer: Shenzhen Ishan Technology Co., Ltd
Category: homeopathic | Type: HUMAN OTC DRUG LABEL
Date: 20260212

ACTIVE INGREDIENTS: CHLORHEXIDINE ACETATE 2 g/100 g
INACTIVE INGREDIENTS: WATER; 2-(TRIFLUOROMETHYL)BENZOIC ACID; ALCOHOL; TRICLOSAN

Active ingredient

Chlorhexidine Acetate 2%

Inactive ingredient

Purified water, Benzoic acid, Boric acid, Ethanol, Triclosan.

Keep out of reach of children.

if swallowed, call poison control or seek medical help.

Stop use and ask a doctor if

pain worsens or persists, or if youexperience any of these symptoms: burning, itching, rash, or other changes in theskin where the product was placed.

USES

Effectively treats nail fungus, discoloration, splitting, thickening, crumbling and brittleness.

Other information

Store at room temperature 59-86°F(15-30°C)

Directions

* Before use, clean the affected area with soap and soak the nail in warm waterto soften it.
* For toenail fungus, scrape the dirt off the nail and gently file the thickened partof the fungal nail until it's flat (be careful not to damage the nail bed).

* Use twice a day, morning and evening.

* Repeat this process 2-3 times a day until a healthy nail begins its gradualregeneration.

* For best results, use continuously for 6 weeks.

Dosage & administration

Apply 2-3 times a day

When using this product

Do not wear this product directly on skin.

Be aware of low-temperature burns.

Warning

Warnings: For external use only

* Do not use on children under 2 years of age unless directed by a doctor.

* Avoid contact with eyes when using this product, if contact occurs rinse thoroughly with water

* Stop use and ask a doctor if
lrritation occurs or discomfort persists.Keep out of reach of children
* If swallowed, call a poison control centre or seek medical attention immediately.

RECENT MAJOR CHANGES

no